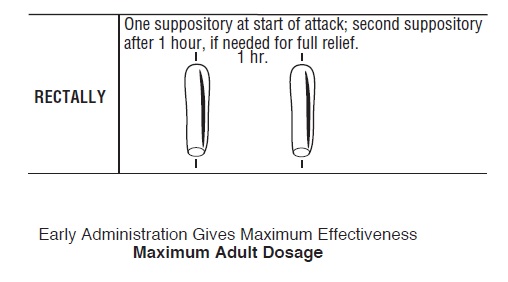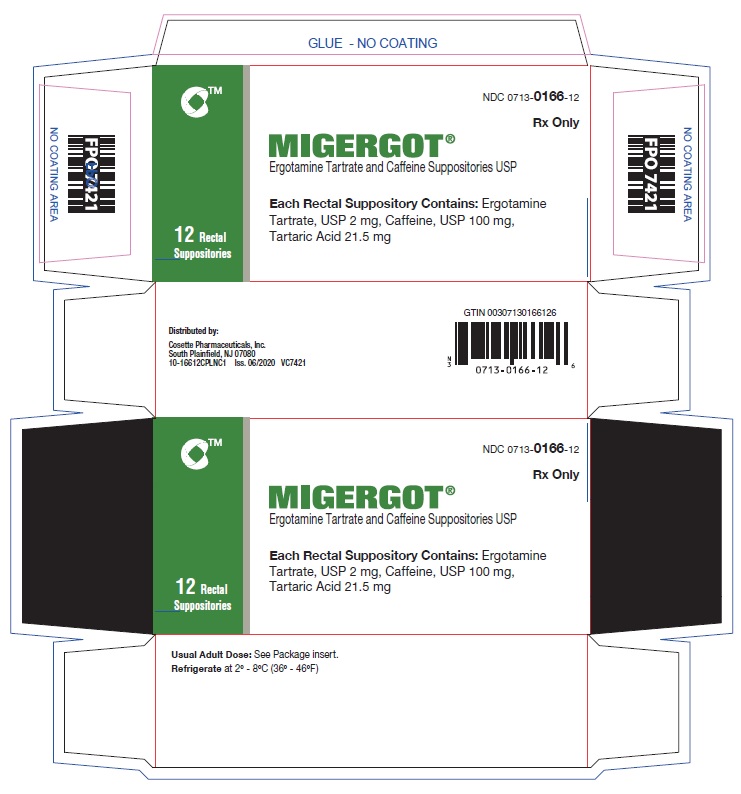 DRUG LABEL: MIGERGOT
NDC: 0713-0166 | Form: SUPPOSITORY
Manufacturer: Cosette Pharmaceuticals, Inc.
Category: prescription | Type: HUMAN PRESCRIPTION DRUG LABEL
Date: 20221129

ACTIVE INGREDIENTS: ERGOTAMINE TARTRATE 2 mg/1 1; CAFFEINE 100 mg/1 1
INACTIVE INGREDIENTS: TARTARIC ACID; HARD FAT

ERGOTAMINE TARTRATE and
CAFFEINE SUPPOSITORIES USP
(For Rectal Administration)
Rx only

WARNING

Serious and/or life-threatening peripheral ischemia has been associated with the coadministration of ergotamine tartrate and caffeine with potent CYP 3A4 inhibitors including protease inhibitors and macrolide antibiotics. Because CYP 3A4 inhibition elevates the serum levels of ergotamine tartrate and caffeine, the risk for vasospasm leading to cerebral ischemia and/or ischemia of the extremities is increased. Hence, concomitant use of these medications is contraindicated. (See also CONTRAINDICATIONS and WARNINGS section)

DESCRIPTION: Ergotamine Tartrate and Caffeine Suppository
ergotamine tartrate USP 2 mg
caffeine USP 100 mg
Inactive Ingredients: tartaric acid NF, and hard fat NF
Ergotamine Tartrate and Caffeine Suppositories are for rectal administration only.
Ergotamine Tartrate and Caffeine Suppositories are sealed in foil to afford protection from leakage. If an unavoidable period of exposure to heat softens the suppository, it should be chilled in ice-cold water to solidify it before removing the foil.

CLINICAL PHARMACOLOGY

Ergotamine is an alpha adrenergic blocking agent with a direct stimulating effect on the smooth muscle of peripheral and cranial blood vessels and produces depression of central vasomotor centers. The compound also has the properties of serotonin antagonism. In comparison to hydrogenated ergotamine, the adrenergic blocking actions are less pronounced and vasoconstrictive actions are greater.

Caffeine, also a cranial vasoconstrictor, is added to further enhance the vasoconstrictive effect without the necessity of increasing ergotamine dosage.

Many migraine patients experience excessive nausea and vomiting during attacks, making it impossible for them to retain any oral medication. In such cases, therefore, the only practical means of medication is through the rectal route where medication may reach the cranial vessels directly, evading the splanchnic vasculature and the liver.

Pharmacokinetics: Interactions

Pharmacokinetic interactions (increased blood levels of ergotamine) have been reported in patients treated orally with ergotamine and macrolide antibiotics (e.g., troleandomycin, clarithromycin, erythromycin), and in patients treated orally with ergotamine and protease inhibitors (e.g. ritonavir) presumably due to inhibition of cytochrome P450 3A metabolism of ergotamine (See CONTRAINDICATIONS). Ergotamine has also been shown to be an inhibitor of cytochrome P450 3A catalyzed reactions. No pharmacokinetic interactions involving other cytochrome P450 isoenzymes are known.

INDICATIONS AND USAGE

Ergotamine Tartrate and Caffeine

Indicated as therapy to abort or prevent vascular headache, e.g., migraine, migraine variants or so-called “histaminic cephalalgia”.

CONTRAINDICATIONS

Coadministration of ergotamine with potent CYP 3A4 inhibitors (ritonavir, nelfinavir, indinavir, erythromycin, clarithromycin, and troleandomycin) has been associated with acute ergot toxicity (ergotism) characterized by vasospasm and ischemia of the extremities (see PRECAUTIONS: Drug Interactions), with some cases resulting in amputation. There have been rare reports of cerebral ischemia in patients on protease inhibitor therapy when ergotamine tartrate and caffeine was coadministered, at least one resulting in death. Because of the increased risk for ergotism and other serious vasospastic adverse events, ergotamine use is contraindicated with these drugs and other potent inhibitors of CYP 3A4 (e.g., ketoconazole, itraconazole) (see WARNINGS: CYP 3A4 Inhibitors).

Ergotamine tartrate and caffeine may cause fetal harm when administered to pregnant women. Ergotamine tartrate and caffeine is contraindicated in women who are or may become pregnant. If this drug is used during pregnancy or if the patient becomes pregnant while taking this product, the patient should be apprised of the potential hazard to the fetus.

Peripheral vascular disease, coronary heart disease, hypertension, impaired hepatic or renal function and sepsis.

Hypersensitivity to any of the components.

WARNINGS

CYP 3A4 Inhibitors (e.g. Macrolide Antibiotics and Protease Inhibitors)

Coadministration of ergotamine with potent CYP 3A4 inhibitors such as protease inhibitors or macrolide antibiotics has been associated with serious adverse events; for this reason, these drugs should not be given concomitantly with ergotamine (See CONTRAINDICATIONS). While these reactions have not been reported with less potent CYP 3A4 inhibitors, there is a potential risk for serious toxicity including vasospasm when these drugs are used with ergotamine. Examples of less potent CYP 3A4 inhibitors include: saquinavir, nefazodone, fluconazole, fluoxetine, grapefruit juice, fluvoxamine, zileuton, metronidazole, and clotrimazole. These lists are not exhaustive, and the prescriber should consider the effects on CYP 3A4 of other agents being considered for concomitant use with ergotamine.

Fibrotic Complications

There have been a few reports of patients on ergotamine tartrate and caffeine therapy developing retroperitoneal and/or pleuropulmonary fibrosis. There have also been rare reports of fibrotic thickening of the aortic, mitral, tricuspid, and/or pulmonary valves with long-term continuous use of ergotamine tartrate and caffeine. Ergotamine tartrate suppositories should not be used for chronic daily administration (see DOSAGE AND ADMINISTRATION).

PRECAUTIONS

General

Although signs and symptoms of ergotism rarely develop even after long term intermittent use of the rectally administered drug, care should be exercised to remain within the limits of recommended dosage.

Ergotism is manifested by intense arterial vasoconstriction, producing signs and symptoms of peripheral vascular ischemia. Ergotamine induces vasoconstriction by a direct action on vascular smooth muscle. In chronic intoxication with ergot derivatives, headache, intermittent claudication, muscle pains, numbness, coldness and pallor of the digits may occur. If the condition is allowed to progress untreated, gangrene can result.

While most cases of ergotism associated with ergotamine treatment result from frank overdosage, some cases have involved apparent hypersensitivity. There are few reports of ergotism among patients taking doses within the recommended limits or for brief periods of time. In rare instances, patients, particularly those who have used the medication indiscriminately over long periods of time, may display withdrawal symptoms consisting of rebound headache upon discontinuation of the drug.

Rare cases of a solitary rectal or anal ulcer have occurred from abuse of ergotamine suppositories usually in higher than recommended doses or with continual use at the recommended dose for many years. Spontaneous healing occurs within usually 4-8 weeks after drug withdrawal.

Information for Patients

Patients should be advised that one suppository of ergotamine tartrate and caffeine should be taken at the first sign of a migraine headache. No more than 2 suppositories should be taken for any single migraine attack. No more than 5 suppositories should be taken during any 7-day period. Administration of Ergotamine Tartrate and Caffeine Suppositories should not exceed the dosing guidelines and should not be used for chronic daily administration (see DOSAGE AND ADMINISTRATION). Ergotamine tartrate and caffeine should be used only for migraine headaches. It is not effective for other types of headaches and it lacks analgesic properties. Patients should be advised to report to the physician immediately any of the following: numbness or tingling in the fingers or toes, muscle pain in the arms and legs, weakness in the legs, pain in the chest or temporary speeding or slowing of the heart rate, swelling or itching.

Drug Interactions

CYP 3A4 Inhibitors (e.g. Macrolide Antibiotics and Protease Inhibitors)

See CONTRAINDICATIONS and WARNINGS.

Ergotamine tartrate and caffeine should not be administered with other vasoconstrictors. Use with sympathomimetics (pressor agents) may cause extreme elevation of blood pressure. The beta-blocker Inderal (propranolol) has been reported to potentiate the vasoconstrictive action of ergotamine tartrate and caffeine by blocking the vasodilating property of epinephrine. Nicotine may provoke vasoconstriction in some patients, predisposing to a greater ischemic response to ergot therapy.

The blood levels of ergotamine-containing drugs are reported to be elevated by the concomitant administration of macrolide antibiotics and vasospastic reactions have been reported with therapeutic doses of the ergotamine-containing drugs when coadministered with these antibiotics.

Pregnancy

Teratogenic Effects

There are no studies on the placental transfer or teratogenicity of the combined products of ergotamine tartrate and caffeine. Caffeine is known to cross the placenta and has been shown to be teratogenic in animals. Ergotamine crosses the placenta in small amounts, although it does not appear to be embryotoxic in this quantity. However, prolonged vasoconstriction of the uterine vessels and/or increased myometrial tone leading to reduced myometrial and placental blood flow may have contributed to fetal growth retardation observed in animals. (See CONTRAINDICATIONS)

Nonteratogenic Effects

Ergotamine tartrate and caffeine is contraindicated in pregnancy due to the oxytocic effects of ergotamine. (See CONTRAINDICATIONS)

Labor and Delivery
Ergotamine tartrate and caffeine is contraindicated in labor and delivery due to its oxytocic effect which is maximal in the third trimester. (See CONTRAINDICATIONS)

Nursing Mothers

Ergot drugs are known to inhibit prolactin but there are no reports of decreased lactation with ergotamine tartrate and caffeine. Ergotamine is excreted in breast milk and may cause symptoms of vomiting, diarrhea, weak pulse and unstable blood pressure in nursing infants. Because of the potential for serious adverse reactions in nursing infants from ergotamine tartrate and caffeine, a decision should be made whether to discontinue nursing or discontinue the drug, taking into account the importance of the drug to the mother.

Pediatric Use

Safety and effectiveness in pediatric patients have not been established.

ADVERSE REACTIONS

Cardiovascular: Vasoconstrictive complications of a serious nature may occur at times. These include ischemia, cyanosis, absence of pulse, cold extremities, gangrene, precordial distress and pain, EKG changes and muscle pains. Although these effects occur most commonly with long-term therapy at relatively high doses, they have also been reported with short-term or normal doses. Other cardiovascular adverse effects include transient tachycardia or bradycardia and hypertension.
Gastrointestinal: Nausea and vomiting; rectal or anal ulcer (from overuse of suppositories).
Neurological: Paresthesias, numbness, weakness, and vertigo.
Allergic: Localized edema and itching.
Fibrotic Complications: (See WARNINGS).

To report SUSPECTED ADVERSE REACTIONS, contact Cosette Pharmaceuticals, Inc. at 1-800-922-1038 or FDA at 1-800-FDA-1088 or www.fda.gov/medwatch.

DRUG ABUSE AND DEPENDENCE

There have been reports of drug abuse and psychological dependence in patients on ergotamine tartrate and caffeine therapy. Due to the chronicity of vascular headaches, it is imperative that patients be advised not to exceed recommended dosages with long-term use to avoid ergotism. (See PRECAUTIONS)

OVERDOSAGE

The toxic effects of an acute overdosage of ergotamine tartrate and caffeine are due primarily to the ergotamine component. The amount of caffeine is such that its toxic effects will be overshadowed by those of ergotamine. Symptoms include vomiting, numbness, tingling, pain and cyanosis of the extremities associated with diminished or absent peripheral pulses; hypertension or hypotension; drowsiness, stupor, coma, convulsions and shock. A case has been reported of reversible bilateral papillitis with ring scotomata in a patient who received five times the recommended daily adult dose over a period of 14 days.

Treatment consists of removal of the offending drug by enema. Maintenance of adequate pulmonary ventilation, correction of hypotension, and control of convulsions and blood pressure are important considerations. Treatment of peripheral vasospasm should consist of warmth, but not heat, and protection of the ischemic limbs. Vasodilators may be beneficial but caution must be exercised to avoid aggravating an already existent hypotension.

DOSAGE AND ADMINISTRATION

Procedure

For best results, dosage should start at the first sign of an attack.

Rectally

Two suppositories is the maximum dose for an individual attack.

Total weekly dosage should not exceed 5 suppositories. Ergotamine Tartrate and Caffeine Suppositories should not be used for chronic daily administration.

In carefully selected patients, with due consideration of maximum dosage recommendations, administration of the drug at bedtime may be an appropriate short-term preventive measure.

HOW SUPPLIED

HOW SUPPLIED: Ergotamine Tartrate and Caffeine Suppositories USP are supplied in boxes of 12 foil wrapped suppositories.
NDC 0713-0166-12

Store and Dispense

The suppositories should be refrigerated at 2° to 8°C (36° to 46°F).
Distributed by:
Cosette Pharmaceuticals, Inc.
South Plainfield, NJ 07080

8-0166CPLNC1 Iss. 06/2020 VC7420

PACKAGE LABEL

NDC 0713-0166-12

MIGERGOT®

Ergotamine Tartrate and Caffeine Suppositories USP

Each Rectal Suppository Contains: Ergotamine Tartrate, USP 2 mg, Caffeine, USP 100 mg, Tartaric Acid 21.5 mg

Usual Adult Dose: See Package insert.

Refrigerate at 2º - 8ºC (36º - 46ºF)

12 Rectal Suppositories Rx Only

Cosette Pharmaceuticals, Inc.